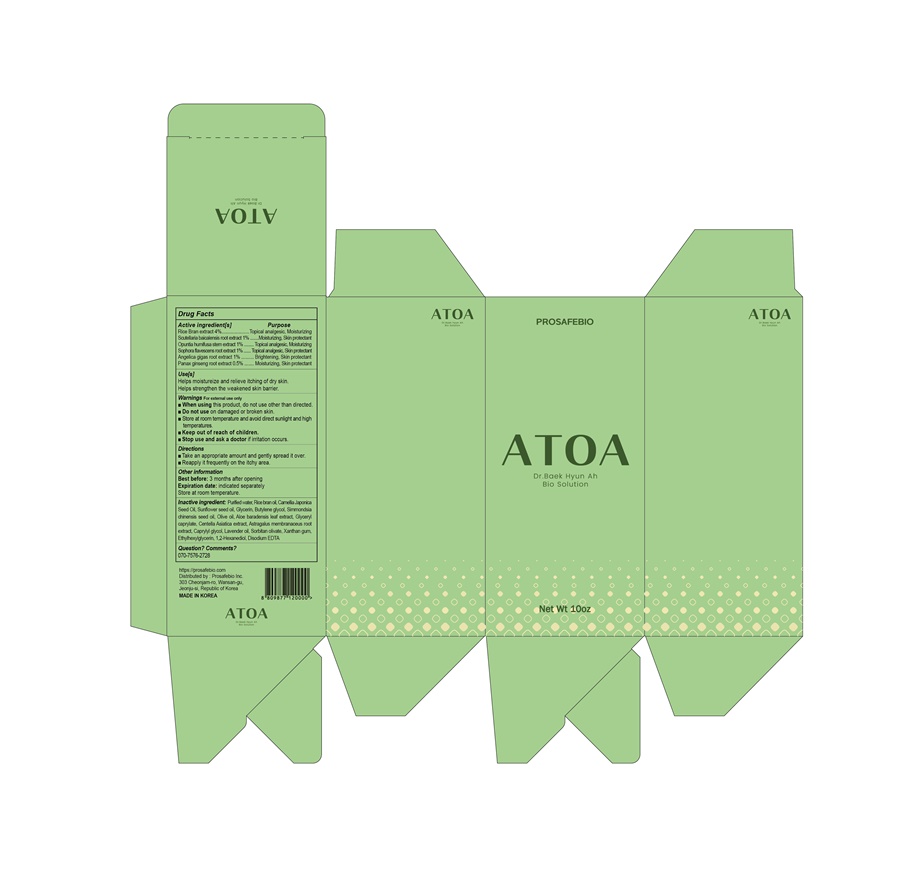 DRUG LABEL: ATOA
NDC: 81745-301 | Form: CREAM
Manufacturer: PROSAFEBIO
Category: otc | Type: HUMAN OTC DRUG LABEL
Date: 20221020

ACTIVE INGREDIENTS: RICE BRAN 4 g/100 mL; SOPHORA FLAVESCENS ROOT 1 g/100 mL; SCUTELLARIA BAICALENSIS ROOT 1 g/100 mL; OPUNTIA HUMIFUSA WHOLE 1 g/100 mL; ANGELICA GIGAS ROOT 1 g/100 mL; ASIAN GINSENG 0.5 g/100 mL
INACTIVE INGREDIENTS: GLYCERIN; XANTHAN GUM; EDETATE DISODIUM ANHYDROUS; CAMELLIA JAPONICA SEED OIL; CAPRYLYL GLYCOL; SORBITAN OLIVATE; SUNFLOWER OIL; BUTYLENE GLYCOL; ALOE VERA LEAF; ASTRAGALUS PROPINQUUS ROOT POLYSACCHARIDES; ETHYLHEXYLGLYCERIN; 1,2-HEXANEDIOL; GLYCERYL CAPRATE; CENTELLA ASIATICA; SIMMONDSIA CHINENSIS SEED; OLIVE OIL; RICE BRAN OIL; WATER; LAVENDER OIL

ATOA
81745-301

purpose

Topical analgesic, Moisturizing, Skin protectant,Brightening

Use

Helps moistureize and relieve itching of dry skin.

Helps strengthen the weakened skin barrier.

Warnings

Do not use on damaged or broken skin.

Warnings

When using this product, do not use other than directed.

Warnings

Stop use and ask a doctor if irritation occurs.

Warnings

For external use only

Store at room temperature and avoid direct sunlight and high temperatures.

Warnings

Keep out of reach of children.

Directions

◾Take an appropriate amount and gently spread it over.

◾Reapply it frequently on the itchy area.

active ingredient

Rice Bran extract

Scutellaria baicalensis root extract

Opuntia humifusa stem extract

Sophora flavescens root extract

Angelica gigas root extract

Panax ginseng root extract

Inactive Ingredients

Purified water, Rice bran oil, Camellia Japonica Seed Oil, Sunflower seed oil, Glycerin, Butylene glycol, Simmondsia chinensis seed oil, Olive oil, Aloe baradensis leaf extract, Glyceryl caprylate, Centella Asiatica extract, Astragalus membranaceus root extract, Caprylyl glycol, Lavender oil, Sorbitan olivate, Xanthan gum, Ethylhexylglycerin, 1,2-Hexanediol, Disodium EDTA

Other information

Best before: 3 months after opening

Expiration date: indicated separately

Store at room temperature.

Question? Comments?

070-7576-2728

https://prosafebio.com

ATOA

LABEL

81745-301